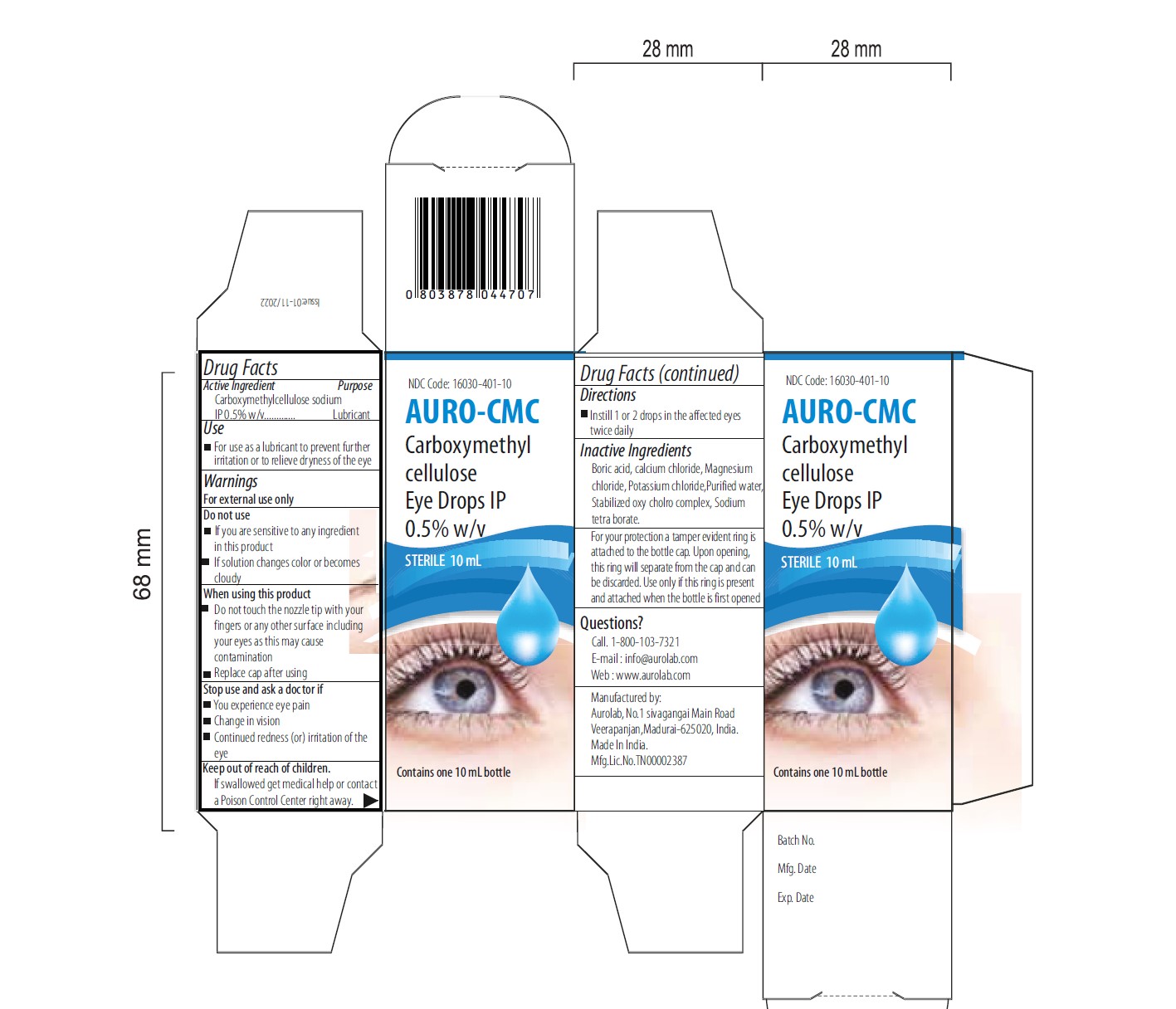 DRUG LABEL: AURO-CMC
NDC: 16030-401 | Form: FOR SOLUTION
Manufacturer: Aurolab
Category: otc | Type: HUMAN OTC DRUG LABEL
Date: 20260127

ACTIVE INGREDIENTS: CARBOXYMETHYLCELLULOSE SODIUM, UNSPECIFIED 5 mg/1 mL
INACTIVE INGREDIENTS: WATER; BORIC ACID; CALCIUM CHLORIDE; MAGNESIUM CHLORIDE; POTASSIUM CHLORIDE; SODIUM BORATE

Active ingredient

Carboxymethylcellulose sodium IP 0.5% w/v

DIRECTIONS FOR USE

- lnstill 1or 2 drops in the affected eye, as needed

INACTIVE INGREDIENT

1. Boric acid
2. Calcium chloride
3. Magnesium chloride
4. Potassium chloride
5. Water
6. Sodium tetra borate

Use

For use as a lubricant to prevent further irritation or to relieve dryness of the eye

Questions

Call. 1-800-103-7321
E-mail : info@aurolab.com
Web : www.aurolab.com

Keep out of reach of children

If swallowed get medical help or contact a Poison Control Center right away

Stop use and ask a doctor if

1.You experience eye pain

2.Change in vision Continued redness (or) irritation of the eye

Do not use

1.If you are sensitive to any ingredient in this product
2.If solution changes color or becomes cloudy

Warnings

For external use only

Indication & usage

Do not touch the nozzle tip to any surface since this may contaminate the solution
Replace cap after using

Dose

Instill 1 or 2 drops in the affected eyes as needed

Eye lubricant